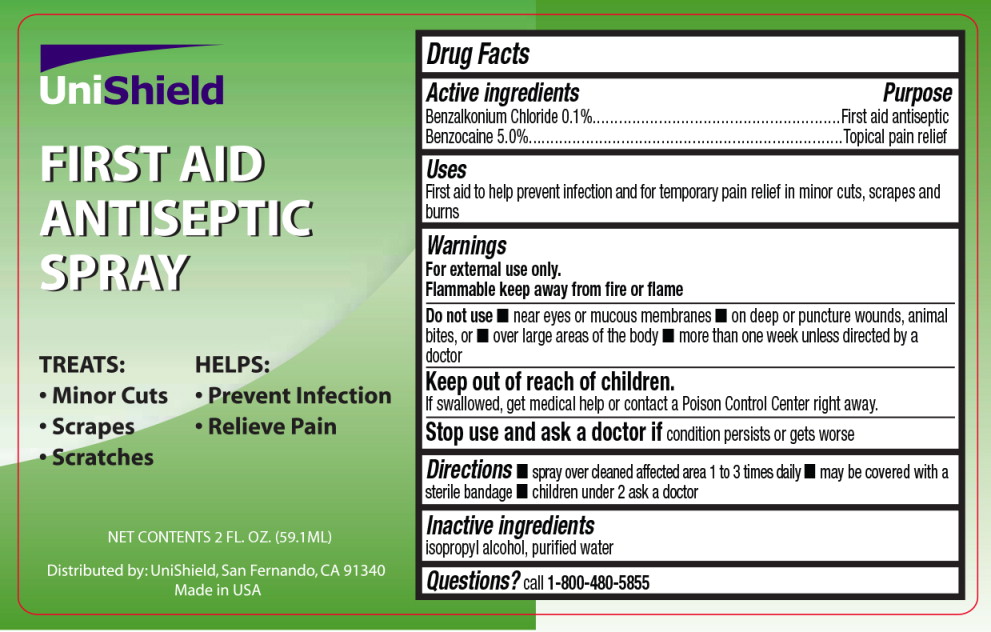 DRUG LABEL: First Aid Antiseptic
NDC: 49314-0098 | Form: SPRAY
Manufacturer: Unishield 
Category: otc | Type: HUMAN OTC DRUG LABEL
Date: 20150127

ACTIVE INGREDIENTS: benzalkonium chloride 1 mg/1 g; benzocaine 50 mg/1 g
INACTIVE INGREDIENTS: isopropyl alcohol; water

Drug Facts

Active ingredients

Benzalkonium Chloride 0.1 %

Benzocaine 5.0%

Purpose

First aid antiseptic

Topical pain relief

Uses

First aid to help prevent infection and for temporary pain relief in minor cuts, scrapes and burns

Warnings

For external use only.

Flammable keep away from fire or flame

Do not use

- near eyes or mucous membranes
- on deep or puncture wounds, animal bites, or
- over large areas of the body
- more than one week unless directed by a doctor

Keep out of reach of children.

If swallowed, get medical help or contact a Poison Control Center right away.

Stop use and ask a doctor if condition persists or gets worse

Directions

- spray over cleaned affected area 1 to 3 times daily
- may be covered with a sterile bandage
- children under 2 ask a doctor

Inactive ingredients

isopropyl alcohol, purified water

Questions?

call 1-800-480-5855

Principal Display Panel - Bottle Label

UniShield

FIRST AID
ANTISEPTIC
SPRAY

TREATS:

- Minor Cuts
- Scrapes
- Scratches

HELPS:

- Prevent Infection
- Relieve Pain

NET CONTENTS 2 FL. OZ. (59.1 ML)

Distributed by: Unishield, San Francisco, CA 91340

Made in USA